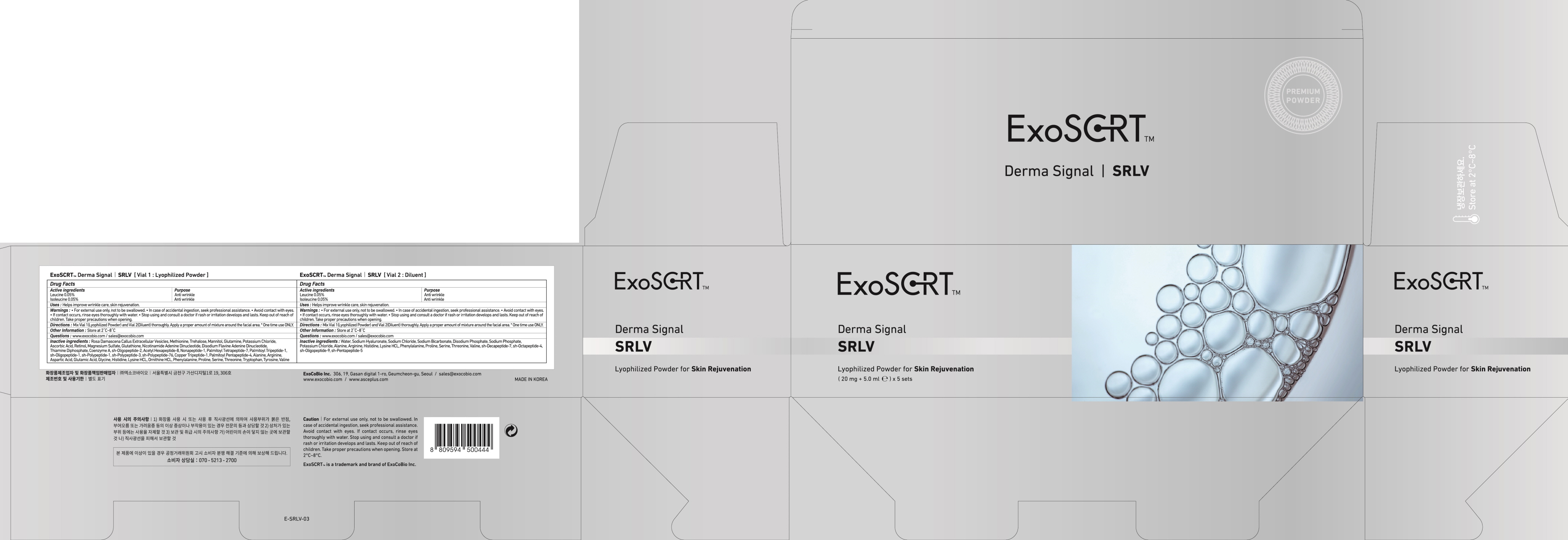 DRUG LABEL: ExoSCRT Derma Signal SRLV Vial 2. Diluent
NDC: 72951-150 | Form: LIQUID
Manufacturer: Exocobio Inc.
Category: otc | Type: HUMAN OTC DRUG LABEL
Date: 20241209

ACTIVE INGREDIENTS: LEUCINE 0.0025 g/5 mL; ISOLEUCINE 0.0025 g/5 mL
INACTIVE INGREDIENTS: WATER; HYALURONATE SODIUM

ACTIVE INGREDIENT

Leucine 0.05%
Isoleucine 0.05%

INACTIVE INGREDIENTS

Water, Sodium Hyaluronate, Sodium Chloride, Sodium Bicarbonate, Disodium Phosphate, Sodium Phosphate, Potassium Chloride, Alanine, Arginine, Histidine, Lysine HCL, Phenylalanine, Proline, Serine, Threonine, Valine, sh-Decapeptide-7, sh-Octapeptide-4, sh-Oligopeptide-9, sh-Pentapeptide-5

PURPOSE

Anti wrinkle

WARNINGS

For external use only, not to be swallowed.
In case of accidental ingestion, seek professional assistance.
Avoid contact with eyes.
If contact occurs, rinse eyes thoroughly with water.
Stop using and consult a doctor if rash or irritation develops and lasts. Keep out of reach of children. Take proper precautions when opening.

KEEP OUT OF REACH OF CHILDREN

Uses

■ Helps improve wrinkle care, skin rejuvenation.

Directions

■ Mix Vial 1(Lyophilized Powder) and Vial 2(Diluent) thoroughly.
Apply a proper amount of mixture around the facial area.
* One time use ONLY.

Other Information

Store at 2℃~8℃

Questions

www.exocobio.com / sales@exocobio.com